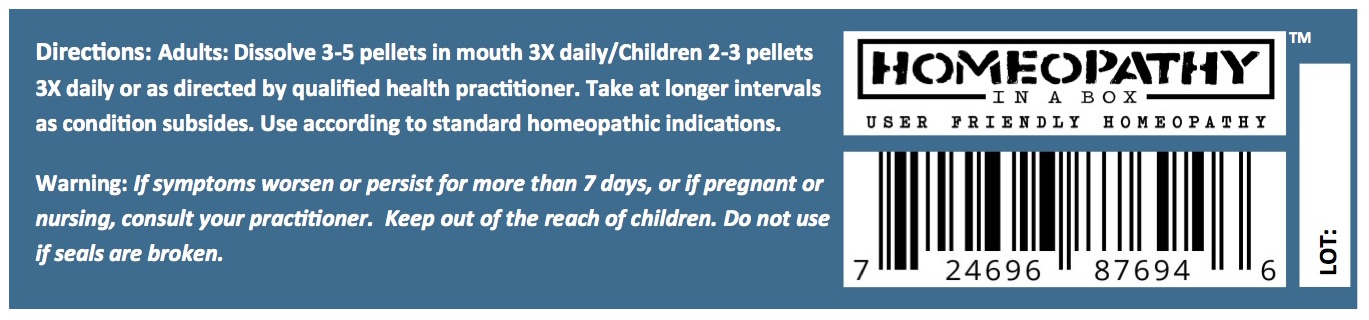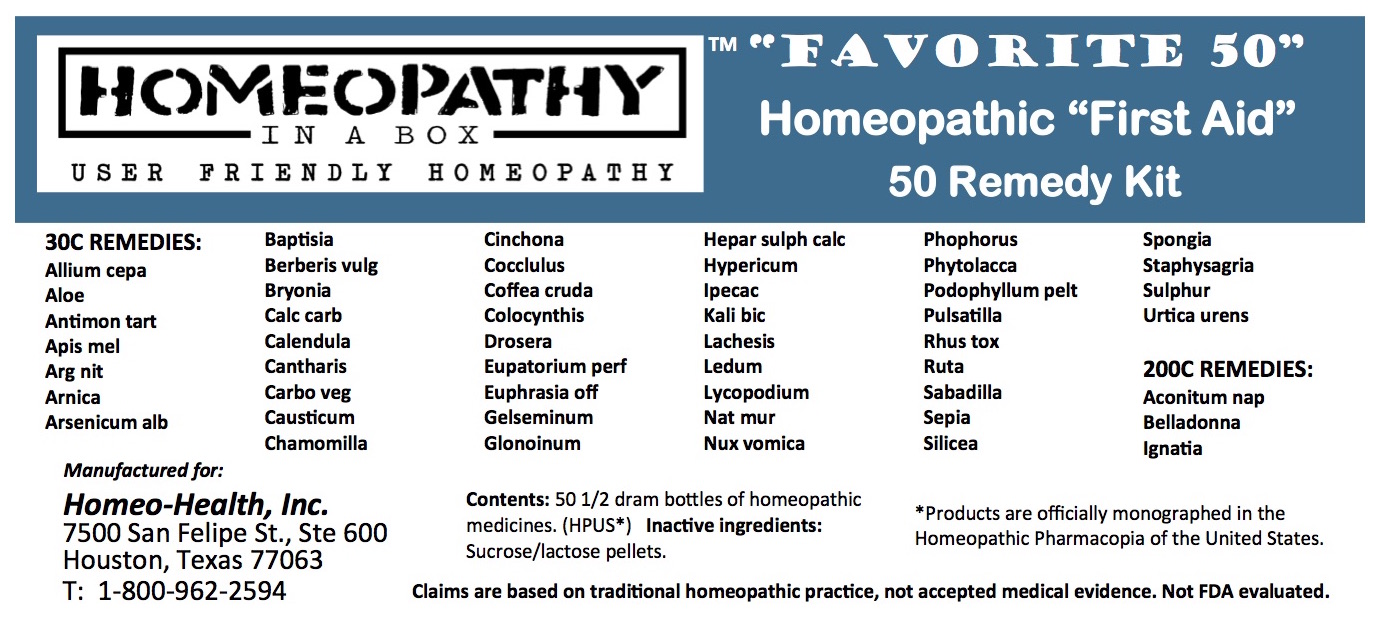 DRUG LABEL: Favorite 50 Homeopathic First Aid Kit
NDC: 60914-002 | Form: PELLET
Manufacturer: Homeopathy in a Box
Category: homeopathic | Type: HUMAN OTC DRUG LABEL
Date: 20180312

ACTIVE INGREDIENTS: CITRULLUS COLOCYNTHIS FRUIT PULP 30 [hp_C]/1 1; EUPHRASIA STRICTA 30 [hp_C]/1 1; CHAMOMILE 30 [hp_C]/1 1; GELSEMIUM SEMPERVIRENS ROOT 30 [hp_C]/1 1; NITROGLYCERIN 30 [hp_C]/1 1; CALCIUM SULFIDE 30 [hp_C]/1 1; HYPERICUM PERFORATUM 30 [hp_C]/1 1; STRYCHNOS IGNATII SEED 200 [hp_C]/1 1; IPECAC 30 [hp_C]/1 1; POTASSIUM DICHROMATE 30 [hp_C]/1 1; LACHESIS MUTA VENOM 30 [hp_C]/1 1; LEDUM PALUSTRE TWIG 30 [hp_C]/1 1; LYCOPODIUM CLAVATUM SPORE 30 [hp_C]/1 1; DROSERA ROTUNDIFOLIA 30 [hp_C]/1 1; PODOPHYLLUM PELTATUM ROOT 30 [hp_C]/1 1; SODIUM CHLORIDE 30 [hp_C]/1 1; STRYCHNOS NUX-VOMICA SEED 30 [hp_C]/1 1; PHOSPHORUS 30 [hp_C]/1 1; PHYTOLACCA AMERICANA ROOT 30 [hp_C]/1 1; PULSATILLA VULGARIS 30 [hp_C]/1 1; SCHOENOCAULON OFFICINALE SEED 30 [hp_C]/1 1; TOXICODENDRON RADICANS LEAF 30 [hp_C]/1 1; RUTA GRAVEOLENS FLOWERING TOP 30 [hp_C]/1 1; SEPIA OFFICINALIS JUICE 30 [hp_C]/1 1; SILICON DIOXIDE 30 [hp_C]/1 1; SPONGIA OFFICINALIS SKELETON, ROASTED 30 [hp_C]/1 1; DELPHINIUM STAPHISAGRIA SEED 30 [hp_C]/1 1; SULFUR 30 [hp_C]/1 1; ALOE VERA LEAF 30 [hp_C]/1 1; EUPATORIUM PERFOLIATUM FLOWERING TOP 30 [hp_C]/1 1; ACONITUM NAPELLUS 200 [hp_C]/1 1; ONION 30 [hp_C]/1 1; ANTIMONY POTASSIUM TARTRATE 30 [hp_C]/1 1; APIS MELLIFERA 30 [hp_C]/1 1; SILVER NITRATE 30 [hp_C]/1 1; ARNICA MONTANA 30 [hp_C]/1 1; ARSENIC TRIOXIDE 30 [hp_C]/1 1; ATROPA BELLADONNA 200 [hp_C]/1 1; BRYONIA ALBA ROOT 30 [hp_C]/1 1; OYSTER SHELL CALCIUM CARBONATE, CRUDE 30 [hp_C]/1 1; URTICA URENS 30 [hp_C]/1 1; CALENDULA OFFICINALIS FLOWERING TOP 30 [hp_C]/1 1; LYTTA VESICATORIA 30 [hp_C]/1 1; ACTIVATED CHARCOAL 30 [hp_C]/1 1; BAPTISIA TINCTORIA 30 [hp_C]/1 1; CAUSTICUM 30 [hp_C]/1 1; BERBERIS VULGARIS ROOT BARK 30 [hp_C]/1 1; CINCHONA OFFICINALIS BARK 30 [hp_C]/1 1; ANAMIRTA COCCULUS SEED 30 [hp_C]/1 1; ARABICA COFFEE BEAN 30 [hp_C]/1 1
INACTIVE INGREDIENTS: SUCROSE; LACTOSE

Favorite 50 Homeopathic First Aid Kit

ACTIVE INGREDIENTS

30c REMEDIES:
Allium cepa
Aloe
Antimonium tartaricum
Apis mellifica
Argentum nitricum
Arnica montana
Arsenicum album
Baptisia tinctoria
Berberis vulgaris
Bryonia
Calcarea carbonica
Calendula officinalis
Cantharis
Carbo vegetabilis
Causticum
Chamomilla
Cinchona Officinalis
Cocculus indicus
Coffea cruda
Colocynthis
Drosera
Eupatorium perf
Euphrasia
Gelsemium
Glonoinum
Hepar sulph calc
Hypericum
Ipecac
Kali bic
Lachesis
Ledum
Lycopodium
Nat mur
Nux vomica
Phosphorus
Phytolacca
Podoph pelt
Pulsatilla
Rhus tox
Ruta
Sabadilla
Sepia
Silicea
Spongia tosta
Staphysagria
Sulphur
Urtica urens

200c REMEDIES:
Aconitum napellus
Belladonna
Ignatia amara

USES

Active Ingredient | Purpose
Aconitum napellus | Fear
Allium cepa | Head cold
Aloe | Diarrhea
Antimonium tartaricum | Loose cough
Apis mellifica | Stings
Argentum nitricum | Impulsiveness
Arnica montana | Bruises
Arsenicum album | Vomiting
Baptisia tinctoria | Flu-like symptoms
Belladonna | Fever
Berberis vulgaris | Skin inflammation
Bryonia | Worse motion
Calcarea carbonica | Overwork
Calendula officinalis | Wounds
Cantharis | Urinary tract
Carbo vegetabilis | Exhaustion
Causticum | Hoarseness
Chamomilla | Irritability
Cinchona Officinalis | Debility
Cocculus indicus | Motion sickness
Coffea cruda | Sleeplessness
Colocynthis | Colic-like pain
Drosera | Cough
Eupatorium perfoliatum | Flu-like symptoms
Euphrasia officinalis | Eye irritation
Gelsemium sempervirens | Lethargy
Glonoinum | Throbbing
Hepar sulphuris calcareum | Croupiness
Hypericum perforatum | Shooting pain
Ignatia amara | Sadness
Ipecacuanha | Nausea
Kali bichromicum | Sinuses
Lachesis mutus | Sore throat
Ledum palustre | Black eyes
Lycopodium clavatum | Digestion
Natrium muriaticum | Sneezing
Nux vomica | Vomiting
Phosphorus | Hoarseness
Phytolacca decandra | Breast pain
Podophyllum peltatum | Diarrhea
Pulsatilla | Weeping
Rhus tox | Better motion
Ruta graveolens | Bruised feeling
Sabadilla | Hay fever
Sepia | Indifference
Silicea | Formation of pus
Spongia tosta | Wheezing
Staphysagria | Anger
Sulphur | Skin problems
Urtica urens | Burns

*Products are officially monographed in the Homeopathic Pharmacopia of the United States (HPUS).

Claims are based on traditional homeopathic practice, not accepted medical evidence. Not FDA evaluated.

KEEP OUT OF REACH OF CHILDREN

Keep out of the reach of children.

INDICATIONS

Use according to traditional homeopathic indications.

STOP USE AND ASK DOCTOR

If symptoms worsen or persist for more than 7 days, or if pregnant or nursing, consult your practitioner.

DIRECTIONS

Directions: Adults: Dissolve 3-5 pellets in mouth 3X daily/Children 2-3 pellets 3X daily or as directed by qualified health practitioner. Take at longer intervals as condition subsides. Use according to standard homeopathic indications.

INACTIVE INGREDIENTS

Sucrose/Lactose

Manufactured for:

Homeo-Health, Inc.

7500 San Felipe St., Ste 600 Houston, Texas 77063
T: 1-800-962-2594